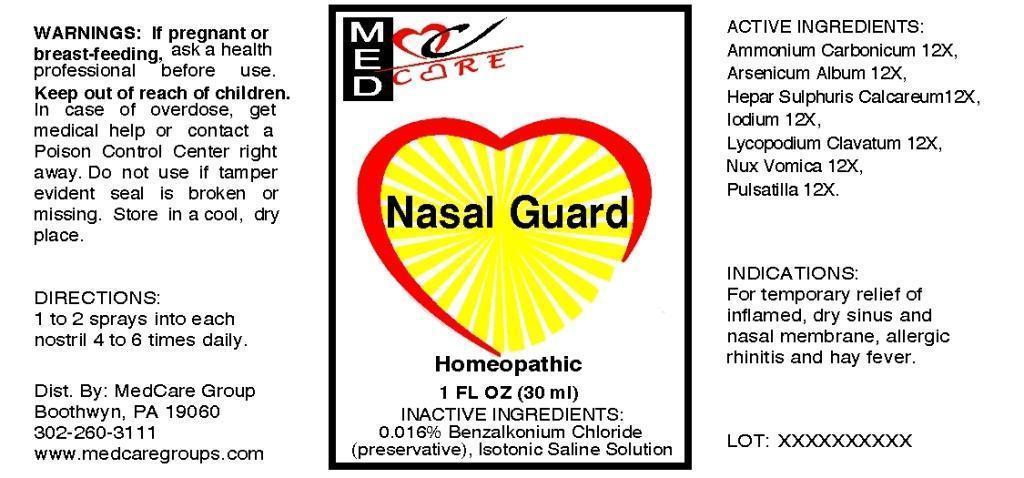 DRUG LABEL: Nasal Guard
NDC: 54557-0003 | Form: LIQUID
Manufacturer: Medcare Group LLC
Category: homeopathic | Type: HUMAN OTC DRUG LABEL
Date: 20130827

ACTIVE INGREDIENTS: AMMONIUM CARBONATE 12 [hp_X]/1 mL; ARSENIC TRIOXIDE 12 [hp_X]/1 mL; CALCIUM SULFIDE 12 [hp_X]/1 mL; IODINE 12 [hp_X]/1 mL; LYCOPODIUM CLAVATUM SPORE 12 [hp_X]/1 mL; STRYCHNOS NUX-VOMICA SEED 12 [hp_X]/1 mL; PULSATILLA VULGARIS 12 [hp_X]/1 mL
INACTIVE INGREDIENTS: BENZALKONIUM CHLORIDE; SODIUM CHLORIDE; WATER

DRUG FACTS:

ACTIVE INGREDIENTS:

Ammonium Carbonicum 12X, Arsenicum Album 12X, Hepar Sulphuris Calcareum 12X, Iodium 12X, Lycopodium Clavatum 12X, Nux Vomica 12X, Pulsatilla 12X.

INDICATIONS:

For temporary relief of inflamed, dry sinus and nasal membrane, allergic rhinitis and hay fever.

WARNINGS:

If pregnant or breast-feeding, ask a health professional before use.

Keep out of reach of children. In case of overdose, get medical help or contact a Poison Control Center right away.

Do not use if tamper evident seal is broken or missing.

Store in a cool, dry place.

Keep out of reach of children. In case of overdose, get medical help or contact a Poison Control Center right away.

DIRECTIONS:

1 to 2 sprays into each nostril 4 to 6 times daily.

INDICATIONS:

For temporary relief of inflamed, dry sinus and nasal membrane, allergic rhinitis and hay fever.

INACTIVE INGREDIENTS:

Benzalkonium Chloride, Isotonic Saline Solution, Demineralized Water

QUESTIONS:

Dist. By: MedCare Group

Boothwyn, PA 19060

302-260-3111

www.medcaregroups.com

PACKAGE DISPLAY LABEL:

MEDCARE

Nasal Guard

Homepathic

1 FL OZ (30 mL)